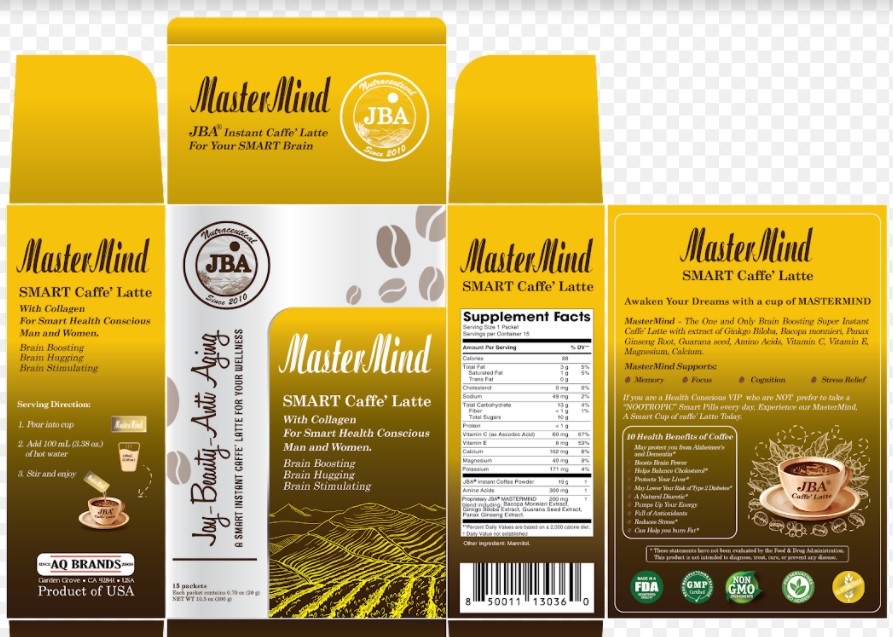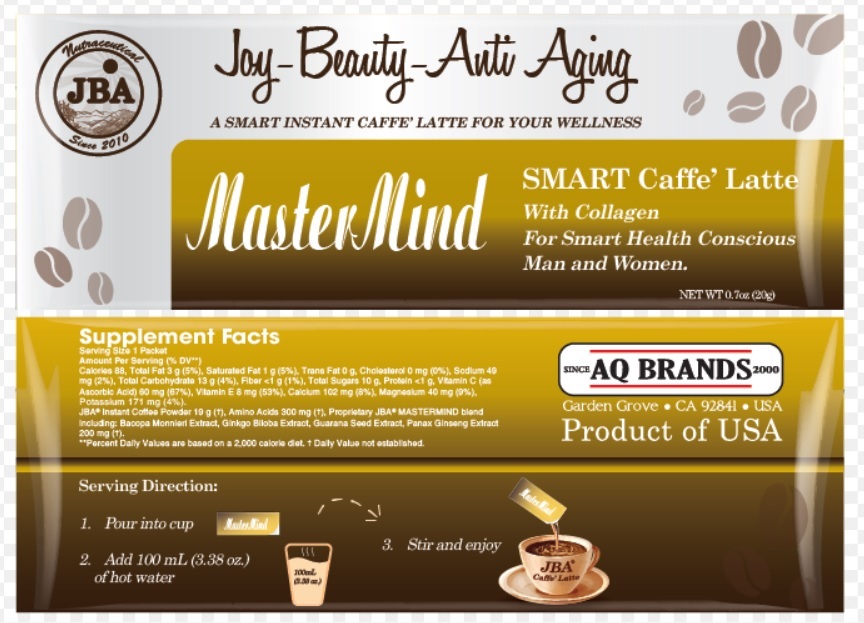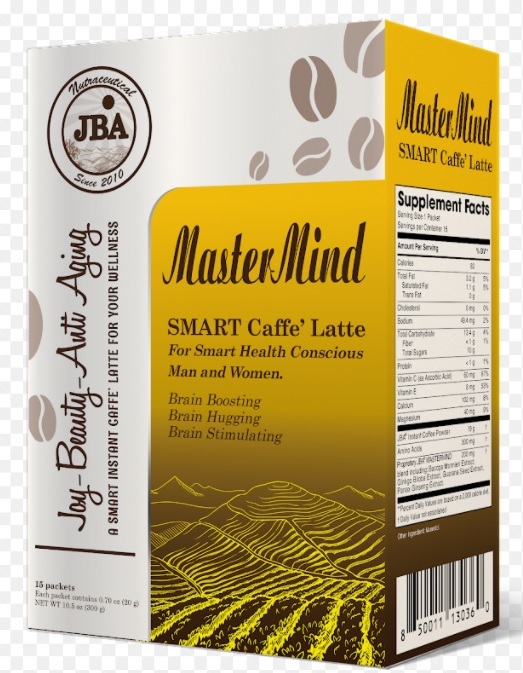 DRUG LABEL: JBA MasterMind SMART Caffe Latte
NDC: 13411-878 | Form: POWDER
Manufacturer: Advanced Pharmaceutical Services, Inc. Dba Affordable Quality Pharmaceuticals
Category: other | Type: DIETARY SUPPLEMENT
Date: 20210913

ACTIVE INGREDIENTS: POTASSIUM 171 mg/20 g; CALCIUM 102 mg/20 g; ASCORBIC ACID 60 mg/20 g; MAGNESIUM 40 mg/20 g; .ALPHA.-TOCOPHEROL 8 mg/20 g; COFFEE BEAN 19 g/20 g; AMINO ACIDS, SOURCE UNSPECIFIED 300 mg/20 g; BACOPA MONNIERI WHOLE 50 mg/20 g; GINKGO 10 mg/20 g; PAULLINIA CUPANA SEED 100 mg/20 g; ASIAN GINSENG 40 mg/20 g
INACTIVE INGREDIENTS: MANNITOL

Identity

Dietary supplement

Direction

1. Pour into cup
2. Add 100 mL (3.38 oz.) of hot water
3. Stir and enjoy.

Safe handling warning

JBA® Mastermind SMART Caffe’ Latte With Collagen For Smart Health Conscious Man and Women
Brain Boosting - Brain Hugging - Brain Stimulating

JBA® Mastermind SMART Caffe’ Latte
Awaken Your Dreams with a cup of MASTERMIND
MasterMind - The One and Only Brain Boosting Super Instant Caffe’ Latte with extract of Ginkgo Biloba, Bacopa monnieri, Panax Ginseng Root, Guarana seed, Amino Acids, Vitamin C, Vitamin E, Magnesium, Calcium.

Master mind supports :

- Memory - Focus - Cognition - Stress Relief

If you are a Health Conscious VIP who are NOT prefer to take a “NOOTROPIC” ” Smart Pills every day, Experience our MasterMind, A Smart Cup of caffe’ Latte Today.

10 Health Benefits of Coffee
- May protect you from Alzheimer’s and Dementia*
- Boosts Brain Power
- Helps Balance Cholesterol*
- Protects Your Liver*
- May Lower Your Risk of Type 2 Diabetes*
- A Natural Diuretic*
- Pumps Up Your Energy
- Full of Antioxidants
- Reduces Stress*
- Can Help you burn Fat*
* These statements have not been evaluated by the Food & Drug Administration. This product is not intended to diagnose, treat, cure, or prevent any disease.